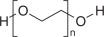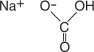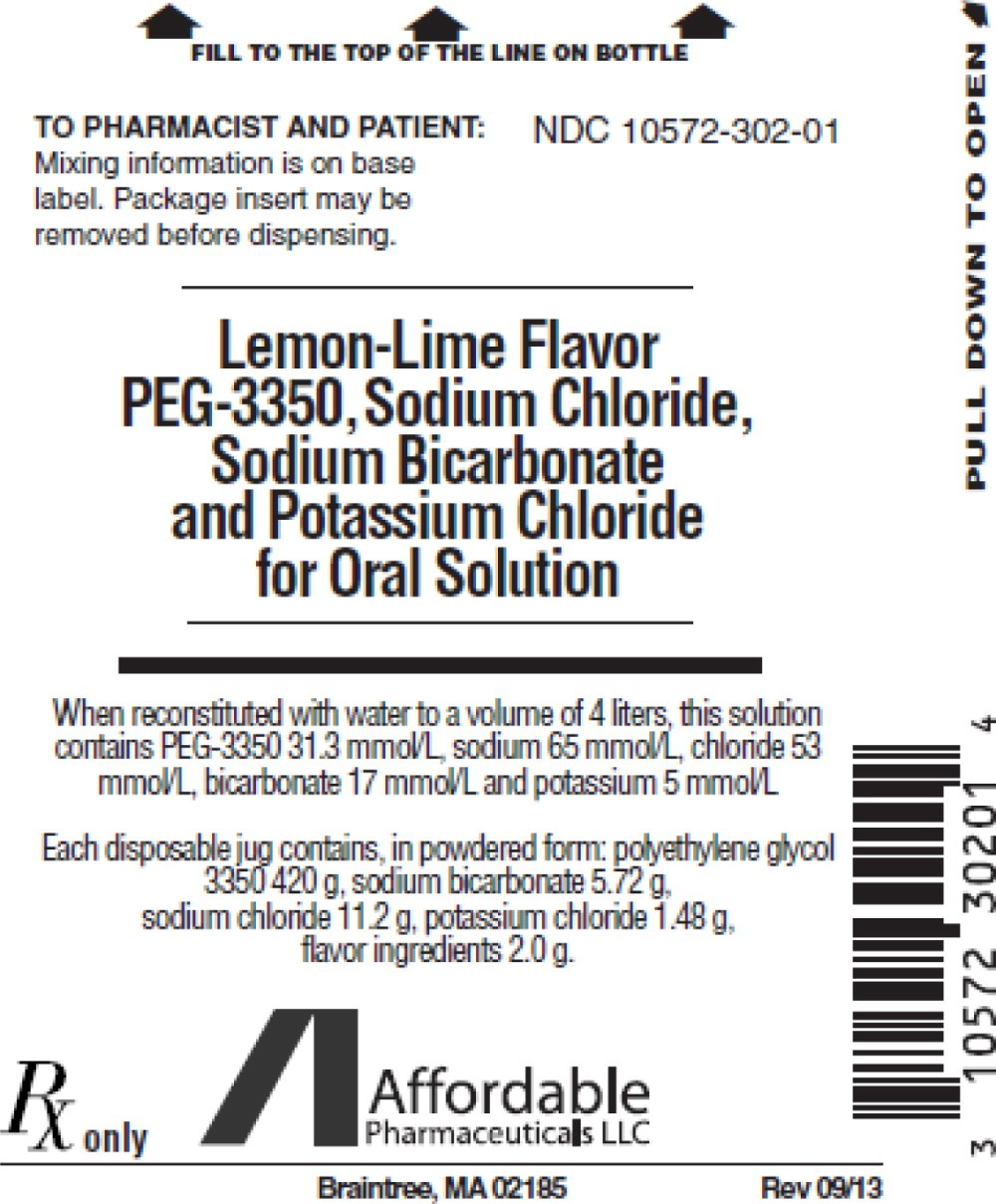 DRUG LABEL: PEG-3350, sodium chloride, sodium bicarbonate and potassium chloride
NDC: 10572-302 | Form: POWDER, FOR SOLUTION
Manufacturer: Affordable Pharmaceuticals, LLC
Category: prescription | Type: HUMAN PRESCRIPTION DRUG LABEL
Date: 20210503

ACTIVE INGREDIENTS: POLYETHYLENE GLYCOL 3350 420 g/4 L; SODIUM CHLORIDE 11.2 g/4 L; SODIUM BICARBONATE 5.72 g/4 L; POTASSIUM CHLORIDE 1.48 g/4 L

HIGHLIGHTS OF PRESCRIBING INFORMATION

These highlights do not include all the information needed to use PEG-3350, sodium chloride, sodium bicarbonate and potassium chloride for oral solution safely and effectively. See full prescribing information for PEG-3350, sodium chloride, sodium bicarbonate and potassium chloride for oral solution.
Polyethylene glycol 3350, sodium chloride, sodium bicarbonate and potassium chloride for oral solution
Initial U.S. Approval: 1991

RECENT MAJOR CHANGES

Warnings and Precautions, Aspiration: (5.7) | 05/2021

1 INDICATIONS AND USAGE

PEG-3350, sodium chloride, sodium bicarbonate and potassium chloride for oral solution is a combination of PEG 3350, an osmotic laxative, and electrolytes indicated for cleansing of the colon in preparation for colonoscopy in adults and pediatric patients aged 6 months or greater (1)

2 DOSAGE AND ADMINISTRATION

- PEG-3350, sodium chloride, sodium bicarbonate and potassium chloride for oral solution, supplied as a powder, must be reconstituted with water before its use (2.1, 5.8)
- On day prior to colonoscopy, instruct patients to:
  - Eat a light breakfast or have clear liquids (avoid red and purple liquids) (2.2).
  - Early in the evening prior to colonoscopy, fill container containing PEG-3350, sodium chloride, sodium bicarbonate and potassium chloride for oral solution powder with lukewarm water to 4 liter fill line (2.2).
  - After capping container, shake vigorously several times (2.2).
- Instruct patients to consume water or clear liquids during and after bowel preparation up until 2 hours before time of colonoscopy (2.3).
- Adults: Drink at a rate of 240 mL (8 oz.) every 10 minutes, until 4 liters are consumed or rectal effluent is clear. For nasogastric tube (NGT), rate is 1.2 to 1.8 liters per hour (2.3)
- Pediatric patients (aged 6 months or greater): Drink 25 mL/kg/hour orally or administer by NGT. Continue drinking until watery stool is clear and free of solid matter (2.3).

3 DOSAGE FORMS AND STRENGTHS

For oral solution: polyethylene glycol 3350 420 grams, sodium bicarbonate 5.72 grams, sodium chloride 11.2 grams, potassium chloride 1.48 grams, and flavoring ingredients 2 grams; supplied in one 4 liter disposable jug (3)

4 CONTRAINDICATIONS

- Gastrointestinal (GI) obstruction, ileus, or gastric retention (4, 5.6)
- Bowel perforation (4, 5.6)
- Toxic colitis or toxic megacolon (4)
- Known allergy or hypersensitivity to components of PEG-3350, sodium chloride, sodium bicarbonate and potassium chloride for oral solution (4, 11)

5 WARNINGS AND PRECAUTIONS

- Risk of fluid and electrolyte abnormalities, arrhythmias, seizures and renal impairment– assess concurrent medications and consider testing in some patients (5.1, 5.2, 5.3, 5.4)
- Patients with renal insufficiency– use caution, ensure adequate hydration and consider testing (5.4)
- Suspected GI obstruction or perforation – rule out the diagnosis before administration (4, 5.6)
- Patients at risk for aspiration – observe during administration (5.7)
- Not for direct ingestion – dilute and take with additional water (5.8)

6 ADVERSE REACTIONS

Most common adverse reactions (≥3%) are: nausea, abdominal fullness and bloating. Abdominal cramps, vomiting and anal irritation occur less frequently (6)

To report SUSPECTED ADVERSE REACTIONS, contact Affordable Pharmaceuticals, LLC at 1-800-514-5617 or FDA at 1-800-FDA-1088 or www.fda.gov/medwatch.

7 DRUG INTERACTIONS

- Some drugs increase risks due to fluid and electrolyte changes (7.1)
- Oral medication taken within 1 hour of start of each dose may not be absorbed properly (7.2)

FULL PRESCRIBING INFORMATION

1 INDICATIONS AND USAGE

PEG-3350, sodium chloride, sodium bicarbonate and potassium chloride for oral solution is indicated for bowel cleansing prior to colonoscopy in adults and pediatric patients aged 6 months or greater.

2 DOSAGE AND ADMINISTRATION

2.1 Dosage Overview

- PEG-3350, sodium chloride, sodium bicarbonate and potassium chloride for oral solution, supplied as a powder, must be reconstituted with water before its use; it is not for direct ingestion [see Dosage and Administration (2.2), Warnings and Precautions (5.8)] .
- Do not reconstitute with other liquids and/or add starch-based thickeners to the mixing container [see Warnings and Precautions (5.7)] .
- The 4-liter reconstituted PEG-3350, sodium chloride, sodium bicarbonate and potassium chloride for oral solution contains: 420 grams of polyethylene glycol (PEG) 3350, 5.72 grams of sodium bicarbonate, 11.2 grams of sodium chloride, 1.4 grams of potassium chloride and 2 grams of flavor ingredients.

2.2 Administration Instructions Prior to Dosage

On the day prior to the colonoscopy, instruct patients to:

1. Take only clear liquids, but avoid red and purple liquids. Patients may consume a light breakfast.
2. Early in the evening prior to colonoscopy, fill the supplied container containing the PEG-3350, sodium chloride, sodium bicarbonate and potassium chloride for oral solution powder with lukewarm water (to facilitate dissolution) to the 4 liter fill line. The solution is clear and colorless when reconstituted to a final volume of 4 liters.
3. After capping the container, shake vigorously several times to ensure that the ingredients are dissolved. When reconstituted use within 48 hours.

2.3 Dosage

The following is the recommended dose of reconstituted PEG-3350, sodium chloride, sodium bicarbonate and potassium chloride for oral solution for adults and pediatric patients ≥ 6 months. Instruct patients they may consume water or clear liquids during the bowel preparation and after completion of the bowel preparation up until 2 hours before the time of the colonoscopy. The solution is more palatable if chilled prior to administration.
• Adults: Instruct patients to drink a total of up to 4 liters at a rate of 240 mL (8 oz.) every 10 minutes, until 4 liters are consumed or the rectal effluent is clear. Rapid drinking of each portion is preferred to drinking small amounts continuously. For NGT, rate is 20-30 mL per minute (1.2 – 1.8 liters per hour).
• Pediatric Patients ≥ 6 Months: Pediatric patients should drink 25 mL/kg/hour until the stool is watery, clear, and free of solid matter. If pediatric patients are unable to drink the reconstituted PEG-3350, sodium chloride, sodium bicarbonate and potassium chloride for oral solution, the solution may be given by nasogastric (NGT). NGT administration is at the rate of 25 mL/kg/hour.

The first bowel movements should occur approximately one hour after the start of PEG-3350, sodium chloride, sodium bicarbonate and potassium chloride for oral solution administration. Continue drinking until the watery stool is clear and free of solid matter.

3 DOSAGE FORMS AND STRENGTHS

For oral solution: One 4 liter jug with powder for reconstitution with water.

Each 4 liter jug contains: polyethylene glycol 3350 420 g, sodium bicarbonate 5.72 g, sodium chloride 11.2 g, potassium chloride 1.48 g and flavoring ingredients 2 g. When made up to 4 liters volume with water, the solution contains PEG-3350 31.3 mmol/L, sodium 65 mmol/L, chloride 53 mmol/L, bicarbonate 17 mmol/L and potassium 5 mmol/L.

4 CONTRAINDICATIONS

PEG-3350, sodium chloride, sodium bicarbonate and potassium chloride for oral solution is contraindicated in the following conditions:

- Gastrointestinal (GI) obstruction, ileus, or gastric retention
- Bowel perforation
- Toxic colitis or toxic megacolon
- Known allergy or hypersensitivity to any component of PEG-3350, sodium chloride, sodium bicarbonate and potassium chloride for oral solution [see How Supplied/Storage and Handling (16)]

5 WARNINGS AND PRECAUTIONS

5.1 Serious Fluid and Serum Chemistry Abnormalities

Advise patients to hydrate adequately before, during, and after the use of PEG-3350, sodium chloride, sodium bicarbonate and potassium chloride for oral solution. Use caution in patients with congestive heart failure when replacing fluids. If a patient develops significant vomiting or signs of dehydration including signs of orthostatic hypotension after taking PEG-3350, sodium chloride, sodium bicarbonate and potassium chloride for oral solution, consider performing post-colonoscopy lab tests (electrolytes, creatinine, and BUN) and treat accordingly. Fluid and electrolyte disturbances can lead to serious adverse events including cardiac arrhythmias, seizures and renal impairment. Fluid and electrolyte abnormalities should be corrected before treatment with PEG-3350, sodium chloride, sodium bicarbonate and potassium chloride for oral solution.

In addition, use caution when prescribing PEG-3350, sodium chloride, sodium bicarbonate and potassium chloride for oral solution for patients who have conditions, or who are using medications, that increase the risk for fluid and electrolyte disturbances or may increase the risk of adverse events of seizure, arrhythmias, and renal impairment [see Drug Interactions (7.1)] .

5.2 Cardiac Arrhythmias

There have been rare reports of serious arrhythmias associated with the use of ionic osmotic laxative products for bowel preparation. Use caution when prescribing PEG-3350, sodium chloride, sodium bicarbonate and potassium chloride for oral solution for patients at increased risk of arrhythmias (e.g., patients with a history of prolonged QT, uncontrolled arrhythmias, recent myocardial infarction, unstable angina, congestive heart failure, or cardiomyopathy). Pre-dose and post-colonoscopy ECGs should be considered in patients at increased risk of serious cardiac arrhythmias.

5.3 Seizures

There have been reports of generalized tonic-clonic seizures and/or loss of consciousness associated with use of bowel preparation products in patients with no prior history of seizures. The seizure cases were associated with electrolyte abnormalities (e.g., hyponatremia, hypokalemia, hypocalcemia, and hypomagnesemia) and low serum osmolality. The neurologic abnormalities resolved with correction of fluid and electrolyte abnormalities.

Use caution when prescribing PEG-3350, sodium chloride, sodium bicarbonate and potassium chloride for oral solution for patients with a history of seizures and in patients at increased risk of seizure, such as patients taking medications that lower the seizure threshold (e.g., tricyclic antidepressants), patients withdrawing from alcohol or benzodiazepines, or patients with known or suspected hyponatremia.

5.4 Renal Impairment

Use caution when prescribing PEG-3350, sodium chloride, sodium bicarbonate and potassium chloride for oral solution for patients with impaired renal function or patients taking concomitant medications that may affect renal function (such as diuretics, angiotensin converting enzyme inhibitors, angiotensin receptor blockers, or non-steroidal anti-inflammatory drugs). Advise these patients of the importance of adequate hydration, and consider performing baseline and post-colonoscopy laboratory tests (electrolytes, creatinine, and BUN) in these patients.

5.5 Colonic Mucosal Ulcerations and Ischemic Colitis

Administration of osmotic laxative products may produce colonic mucosal aphthous ulcerations, and there have been reports of more serious cases of ischemic colitis requiring hospitalization. Concurrent use of stimulant laxatives and PEG-3350, sodium chloride, sodium bicarbonate and potassium chloride for oral solution may increase this risk. The potential for mucosal ulcerations resulting from the bowel preparation should be considered when interpreting colonoscopy findings in patients with known or suspect inflammatory bowel disease (IBD).

5.6 Use in Patients with Significant Gastrointestinal Disease

If gastrointestinal obstruction or perforation is suspected, perform appropriate diagnostic studies to rule out these conditions before administering PEG-3350, sodium chloride, sodium bicarbonate and potassium chloride for oral solution. If a patient experiences severe bloating, distention or abdominal pain, administration should be slowed or temporarily discontinued until the symptoms abate. If gastrointestinal obstruction or perforation is suspected, appropriate studies should be performed to rule out these conditions before administration of PEG-3350, sodium chloride, sodium bicarbonate and potassium chloride for oral solution.
Use with caution in patients with severe active ulcerative colitis.

5.7 Aspiration

Use with caution in patients with impaired gag reflex, unconscious, or semiconscious patients, and patients prone to regurgitation or aspiration. Such patients should be observed during administration of PEG-3350, sodium chloride, sodium bicarbonate and potassium chloride for oral solution, especially if it is administered via nasogastric tube.

Do not combine PEG-3350, sodium chloride, sodium bicarbonate and potassium chloride for oral solution with starch-based thickeners [see Dosage and Administration (2.1)] . Polyethylene glycol (PEG), a component of PEG-3350, sodium chloride, sodium bicarbonate and potassium chloride for oral solution, when mixed with starch-thickened liquids reduces the viscosity of the starch-thickened liquid. When a PEG-based product used for another indication was mixed in starch-based pre-thickened liquids used in patients with dysphagia, thinning of the liquid occurred and cases of choking and potential aspiration were reported.

5.8 Not for Direct Ingestion

The contents of each jug must be diluted with water to a final volume of 4 liters (4 L) and ingestion of additional water is important to patient tolerance. Direct ingestion of the undissolved powder may increase the risk of nausea, vomiting, dehydration, and electrolyte disturbances.

6 ADVERSE REACTIONS

The following serious or otherwise important adverse reactions are described elsewhere in the labeling:

- Serious Fluid and Serum Chemistry Abnormalities [see Warnings and Precautions (5.1)] .
- Cardiac Arrhythmias [see Warnings and Precautions (5.2)] .
- Seizures [see Warnings and Precautions (5.3)] .
- Renal Impairment [see Warnings and Precautions (5.4)]
- Colonic Mucosal Ulcerations, Ischemic Colitis and Ulcerative Colitis [see Warnings and Precautions (5.5)]
- Patients with Significant Gastrointestinal Disease [see Warnings and Precautions (5.6)]
- Aspiration [see Warnings and Precautions (5.7)]
- Direct Ingestion [see Warnings and Precautions (5.8)] .

The following adverse reactions have been identified during post-approval use of PEG-3350, sodium chloride, sodium bicarbonate and potassium chloride for oral solution. Because these reactions are reported voluntarily from a population of uncertain size, it is not always possible to reliably estimate their frequency or establish a causal relationship to drug exposure.

Nausea, abdominal fullness and bloating are the most common adverse reactions (occurred in up to 50% of patients) to administration of PEG-3350, sodium chloride, sodium bicarbonate and potassium chloride for oral solution. Abdominal cramps, vomiting and anal irritation occur less frequently. These adverse reactions are transient and usually subside rapidly. Isolated cases of urticaria, rhinorrhea, dermatitis and (rarely) anaphylactic reaction have been reported which may represent allergic reactions.

Published literature contains isolated reports of serious adverse reactions following the administration of PEG-electrolyte solution products in patients over 60 years of age. These adverse events include upper GI bleeding from Mallory-Weiss Tear, esophageal perforation, asystole, sudden dyspnea with pulmonary edema, and “butterfly-like” infiltrates on chest X-ray after vomiting and aspirating PEG.

7 DRUG INTERACTIONS

7.1 Drugs that May Lead to Fluid and Electrolyte Abnormalities

Use caution when prescribing PEG-3350, sodium chloride, sodium bicarbonate and potassium chloride for oral solution for patients who are using medications that increase the risk for fluid and electrolyte disturbances or may increase the risk of adverse events of seizure, arrhythmias, and prolonged QT in the setting of fluid and electrolyte abnormalities. Consider additional patient evaluations as appropriate [ see Warnings and Precautions (5.1, 5.2, 5.3, and 5.4) ] in patients taking these concomitant medications.

7.2 Potential for Altered Drug Absorption

Oral medication administered within one hour of the start of administration of PEG-3350, sodium chloride, sodium bicarbonate and potassium chloride for oral solution may be flushed from the gastrointestinal tract and the medication may not be absorbed properly.

7.3 Stimulant Laxatives

Concurrent use of stimulant laxatives and PEG-3350, sodium chloride, sodium bicarbonate and potassium chloride for oral solution may increase the risk of mucosal ulceration or ischemic colitis. Avoid use of stimulant laxatives (e.g., bisacodyl, sodium picosulfate) while taking PEG-3350, sodium chloride, sodium bicarbonate and potassium chloride for oral solution.

8 USE IN SPECIFIC POPULATIONS

8.1 Pregnancy

Animal reproduction studies have not been conducted with PEG-3350, sodium chloride, sodium bicarbonate and potassium chloride for oral solution. It is also not known whether PEG-3350, sodium chloride, sodium bicarbonate and potassium chloride for oral solution can cause fetal harm when administered to a pregnant woman or can affect reproductive capacity. PEG-3350, sodium chloride, sodium bicarbonate and potassium chloride for oral solution should be given to a pregnant woman only if clearly needed.

8.3 Nursing Mothers

It is not known whether this drug is excreted in human milk. Because many drugs are excreted in human milk, caution should be exercised when PEG-3350, sodium chloride, sodium bicarbonate and potassium chloride for oral solution is administered to a nursing woman.

8.4 Pediatric Use

Safety and effectiveness of PEG-3350, sodium chloride, sodium bicarbonate and potassium chloride for oral solution in pediatric patients aged 6 months and older is supported by evidence from adequate and well-controlled clinical trials of PEG-3350, sodium chloride, sodium bicarbonate and potassium chloride for oral solution in adults with additional safety and efficacy data from published studies of similar formulations. Use of PEG-3350, sodium chloride, sodium bicarbonate and potassium chloride for oral solution in children younger than 2 years of age should be carefully monitored for occurrence of possible hypoglycemia, as this solution has no caloric substrate. Dehydration has been reported in one child and hypokalemia has been reported in 3 children.

8.5 Geriatric Use

Clinical studies of PEG-3350, sodium chloride, sodium bicarbonate and potassium chloride for oral solution did not include sufficient numbers of subjects aged 65 and over to determine whether they respond differently from younger subjects. Other reported clinical experience has not identified differences in responses between the elderly and younger patients.

11 DESCRIPTION

For oral solution: Each 4 liter (4L) PEG-3350, sodium chloride, sodium bicarbonate and potassium chloride for oral solution jug contains a white powder for reconstitution. PEG-3350, sodium chloride, sodium bicarbonate and potassium chloride for oral solution is a combination of polyethylene glycol 3350, an osmotic laxative, and electrolytes (sodium chloride, sodium bicarbonate and potassium chloride) for oral solution.

Each 4 liter jug contains: polyethylene glycol 3350 420 g, sodium bicarbonate 5.72 g, sodium chloride 11.2 g, potassium chloride 1.4 g. The solution is clear and colorless when reconstituted to a final volume of 4 liters with water.

Polyethylene Glycol 3350, USP

Sodium Bicarbonate, USP

The chemical name is NaHCO3. The average Molecular Weight is 84.01. The structural formula is:

Sodium Chloride, USP

The chemical name is NaCl. The average Molecular Weight: 58.44. The structural formula is:

Na^+ Cl^-

Potassium Chloride, USP

The chemical name is KCl. The average Molecular Weight: 74.55. The structural formula is:

K-Cl

12 CLINICAL PHARMACOLOGY

12.1 Mechanism of Action

The primary mode of action is thought to be through the osmotic effect of polyethylene glycol 3350 which causes water to be retained in the colon and produces a watery stool.

12.2 Pharmacodynamics

PEG-3350, sodium chloride, sodium bicarbonate and potassium chloride for oral solution induces as diarrhea which rapidly cleanses the bowel, usually within four hours.

12.3 Pharmacokinetics

The pharmacokinetics of PEG3350 following administration of PEG-3350, sodium chloride, sodium bicarbonate and potassium chloride for oral solution were not assessed. Available pharmacokinetic information for oral PEG3350 suggests that it is poorly absorbed.

13 NONCLINICAL TOXICOLOGY

13.1 Carcinogenesis, Mutagenesis, Impairment of Fertility

Long term studies in animals have not been performed to evaluate carcinogenic potential of PEG-3350, sodium chloride, sodium bicarbonate and potassium chloride for oral solution. Studies to evaluate the possible impairment of fertility or mutagenic potential of PEG-3350, sodium chloride, sodium bicarbonate and potassium chloride for oral solution have not been performed.

16 HOW SUPPLIED/STORAGE AND HANDLING

In powdered form, for oral administration as a solution following reconstitution.

PEG-3350, sodium chloride, sodium bicarbonate and potassium chloride for oral solution is available in a disposable jug in powdered form containing:

Lemon-Lime Flavor PEG-3350, sodium chloride, sodium bicarbonate and potassium chloride for oral solution: polyethylene glycol 3350 420 g, sodium bicarbonate 5.72 g, sodium chloride 11.2 g, potassium chloride 1.48 g and flavoring ingredients 2.0 g. When made up to 4 liters volume with water, the solution contains PEG-3350 31.3 mmol/L, sodium 65 mmol/L, chloride 53 mmol/L, bicarbonate 17 mmol/L and potassium 5 mmol/L.

Storage:

Store at 25°C (77°F); excursions permitted to 15-30°C (59-86°F) [see USP Controlled Room Temperature]. When reconstituted, keep solution refrigerated. Use within 48 hours. Discard unused portion.
Keep out of reach of children.

Lemon-Lime Flavor PEG-3350, sodium chloride,
sodium bicarbonate and potassium chloride for oral solution NDC 10572-302-01

17 PATIENT COUNSELING INFORMATION

See FDA-Approved Patient Labeling (Medication Guide). Instruct patients:

- To let you know if they have trouble swallowing or are prone to regurgitation or aspiration.
- Not to take other laxatives while they are taking PEG-3350, sodium chloride, sodium bicarbonate and potassium chloride for oral solution.
- To consume water or clear liquids during the bowel preparation and after completion of the bowel preparation up until 2 hours before the time of the colonoscopy.
- That if they experience severe bloating, distention or abdominal pain, the administration of the solution should be slowed or temporarily discontinued until the symptoms abate. Advise patients to report these events to their health care provider.
- That if they have hives, rashes, or any allergic reaction, they should discontinue the medication and contact their health care provider. Medication should be discontinued until they speak to their physician.
- To contact their healthcare provider if they develop signs and symptoms of dehydration. [see Warnings and Precautions (5.1)] .
- That oral medication administered within one hour of the start of administration of PEG-3350, sodium chloride, sodium bicarbonate and potassium chloride for oral solution may be flushed from the GI tract and the medication may not be absorbed completely.

Distributed by Affordable Pharmaceuticals, LLC, Braintree, MA 02185

Medication Guide

PEG-3350, sodium chloride, sodium bicarbonate and potassium chloride for oral solution (PEG-3350, so-DEE-um klor-IDE, so-DEE-um bi-CAR-bon-ate and po-TASS-ee-um klor-IDE for oral solution)

Read this Medication Guide before you start taking PEG-3350, sodium chloride, sodium bicarbonate and potassium chloride for oral solution. This information does not take the place of talking with your healthcare provider about your medical condition or your treatment.

What is the most important information I should know about PEG-3350, sodium chloride, sodium bicarbonate and potassium chloride for oral solution?

PEG-3350, sodium chloride, sodium bicarbonate and potassium chloride for oral solution and other osmotic bowel preparations can cause serious side effects, including:

Serious loss of body fluid (dehydration) and changes in blood salts (electrolytes) in your blood.

These changes can cause:

- abnormal heartbeats that can cause death
- seizures. This can happen even if you have never had a seizure.
- kidney problems

Your chance of having fluid loss and changes in body salts with PEG-3350, sodium chloride, sodium bicarbonate and potassium chloride for oral solution is higher if you:

- have heart problems
- have kidney problems
- take water pills or non-steroidal anti-inflammatory drugs (NSAIDS)

Tell your healthcare provider right away if you have any of these symptoms of a loss of too much body fluid (dehydration) while taking PEG-3350, sodium chloride, sodium bicarbonate and potassium chloride for oral solution:

- vomiting that prevents you from keeping down the solution
- dizziness
- urinating less often than normal
- headache

See Section "What are the possible side effects of PEG-3350, sodium chloride, sodium bicarbonate and potassium chloride for oral solution” for more information about side effects.

What is PEG-3350, sodium chloride, sodium bicarbonate and potassium chloride for oral solution?

PEG-3350, sodium chloride, sodium bicarbonate and potassium chloride for oral solution is a prescription medicine used by adults to clean the colon before a colonoscopy. PEG-3350, sodium chloride, sodium bicarbonate and potassium chloride for oral solution cleans your colon by causing you to have diarrhea. Cleaning your colon helps your healthcare provider see the inside of your colon more clearly during your colonoscopy.

PEG-3350, sodium chloride, sodium bicarbonate and potassium chloride for oral solution is safe and effective for use in pediatric patients aged 6 months and older.

Who should not take PEG-3350, sodium chloride, sodium bicarbonate and potassium chloride for oral solution?

Do not take PEG-3350, sodium chloride, sodium bicarbonate and potassium chloride for oral solution if your heathcare provider has told you that you have:

- a blockage in your bowel (obstruction)
- an opening in the wall of your stomach or intestine (bowel perforation)
- problems with food and fluid emptying from your stomach (gastric retention)
- a very dilated intestine (bowel)
- an allergy to any of the ingredients in PEG-3350, sodium chloride, sodium bicarbonate and potassium chloride for oral solution. See the end of this leaflet for a complete list of ingredients in PEG-3350, sodium chloride, sodium bicarbonate and potassium chloride for oral solution.

What should I tell my healthcare provider before taking PEG-3350, sodium chloride, sodium bicarbonate and potassium chloride for oral solution?

Before you take PEG-3350, sodium chloride, sodium bicarbonate and potassium chloride for oral solution, tell your healthcare provider if you:

- have heart problems
- have stomach or bowel problems
- have ulcerative colitis
- have problems with swallowing or gastric reflux
- have a history of seizures
- are withdrawing from drinking alcohol
- have a low blood salt (sodium) level
- have kidney problems
- any other medical conditions
- are pregnant. It is not known if PEG-3350, sodium chloride, sodium bicarbonate and potassium chloride for oral solution will harm your unborn baby. Talk to your doctor if you are pregnant or plan to become pregnant.
- are breastfeeding or plan to breastfeed. It is not known if PEG-3350, sodium chloride, sodium bicarbonate and potassium chloride for oral solution passes into your breast milk. You and your healthcare provider should decide if you will take PEG3350, sodium chloride, sodium bicarbonate and potassium chloride for oral solution while breastfeeding.

Tell your healthcare provider about all the medicines you take, including prescription and non-prescription medicines, vitamins, and herbal supplements.

PEG-3350, sodium chloride, sodium bicarbonate and potassium chloride for oral solution may affect how other medicines work. Medicines taken by mouth may not be absorbed properly when taken within 1 hour before the start of PEG-3350, sodium chloride, sodium bicarbonate and potassium chloride for oral solution.

Especially tell your healthcare provider if you take:

- medicines for blood pressure or heart problems
- medicines for kidney problems
- medicines for seizures
- water pills (diuretics)
- non-steroidal anti-inflammatory medicines (NSAID) pain medicines
- laxatives
- starch-based thickeners. For patients who have trouble swallowing, do not mix PEG-3350, sodium chloride, sodium bicarbonate and potassium chloride for oral solution with starch-based thickeners.

Ask your healthcare provider or pharmacist for a list of these medicines if you are not sure if you are taking any of the medicines listed above.

Know the medicines you take. Keep a list of them to show your healthcare provider and pharmacist when you get a new medicine.

How should I take PEG-3350, sodium chloride, sodium bicarbonate and potassium chloride for oral solution?

You must read, understand, and follow these instructions to take PEG-3350, sodium chloride, sodium bicarbonate and potassium chloride for oral solution the right way.

- Take PEG-3350, sodium chloride, sodium bicarbonate and potassium chloride for oral solution exactly as your healthcare provider tells you to take it.
- Drink 240 mL (8 oz.) every 10 minutes. Rapid drinking of each portion is better than drinking small amounts.
- The first bowel movement should occur approximately one hour after you start drinking the solution.
- You may experience some abdominal bloating and distention before the bowels start to move. If severe discomfort or distention occur, stop drinking temporarily or drink each portion at longer intervals until the discomfort goes away.
- Continue drinking until the watery stool is clear and free of solid matter. This usually requires 3 liters and it is best to drink all of the solution.
- Do not take undissolved PEG-3350, sodium chloride, sodium bicarbonate and potassium chloride for oral solution powder that has not been mixed with water (diluted), it may increase your risk of nausea, vomiting and fluid loss (dehydration).
- Each jug of PEG-3350, sodium chloride, sodium bicarbonate and potassium chloride for oral solution must be reconstituted with water (diluted) to 4 liters total volume before drinking.
- Do not take other laxatives while taking PEG-3350, sodium chloride, sodium bicarbonate and potassium chloride for oral solution.
- Do not eat solid foods on the day before your colonoscopy and until after your colonoscopy.Drink only clear liquids:
  - the day before your colonoscopy
  - while taking PEG-3350, sodium chloride, sodium bicarbonate and potassium chloride for oral solution
  - after taking PEG-3350, sodium chloride, sodium bicarbonate and potassium chloride for oral solution until 2 hours before your colonoscopy

What are the possible side effects of PEG-3350, sodium chloride, sodium bicarbonate and potassium chloride for oral solution?

PEG-3350, sodium chloride, sodium bicarbonate and potassium chloride for oral solution can cause serious side effects, including:

- See Section “What is the most important information I should know about PEG-3350, sodium chloride, sodium bicarbonate and potassium chloride for oral solution?”
- changes in certain blood tests. Your healthcare provider may do blood tests after you take PEG-3350, sodium chloride, sodium bicarbonate and potassium chloride for oral solution to check your blood for changes. Tell your healthcare provider if you have any symptoms of too much fluid loss, including:
  - vomiting
  - nausea
  - bloating
  - dizziness
  - stomach (abdominal) cramping
  - headache
  - urinate less than usual
  - trouble drinking clear liquid
- heart problems. PEG-3350, sodium chloride, sodium bicarbonate and potassium chloride for oral solution may cause irregular heartbeats.
- seizures
- ulcers of the bowel or bowel problems (ischemic colitis). Tell your healthcare provider right away if you have severe stomach-area (abdomen) pain or rectal bleeding.

The most common side effects of PEG-3350, sodium chloride, sodium bicarbonate and potassium chloride for oral solution include:

- nausea
- stomach (abdominal) fullness
- bloating
- stomach (abdominal) cramps
- vomiting
- anal irritation

Tell your healthcare provider if you have any side effect that bothers you or that does not go away.

These are not all the possible side effects of PEG-3350, sodium chloride, sodium bicarbonate and potassium chloride for oral solution. For more information, ask your healthcare provider or pharmacist.

Call your doctor for medical advice about side effects. You may report side effects to FDA at 1-800-FDA-1088.

How should I store PEG-3350, sodium chloride, sodium bicarbonate and potassium chloride for oral solution?

- Store PEG-3350, sodium chloride, sodium bicarbonate and potassium chloride for oral solution at room temperature, between 59°F to 86°F (15°C to 30°C).
  Keep PEG-3350, sodium chloride, sodium bicarbonate and potassium chloride for oral solution and all medicines out of the reach of children.

General information about the safe and effective use of PEG-3350, sodium chloride, sodium bicarbonate and potassium chloride for oral solution.

Medicines are sometimes prescribed for purposes other than those listed in a Medication Guide. Do not use PEG-3350, sodium chloride, sodium bicarbonate and potassium chloride for oral solution for a condition for which it was not prescribed. Do not give PEG-3350, sodium chloride, sodium bicarbonate and potassium chloride for oral solution to other people, even if they are going to have the same procedure you are. It may harm them.

This Medication Guide summarizes important information about PEG-3350, sodium chloride, sodium bicarbonate and potassium chloride for oral solution. If you would like more information, talk with your healthcare provider. You can ask your pharmacist or healthcare provider for information that is written for healthcare professionals.

For more information, go to www.affordablepharm.com or call 1-800-514-5617.

What are the ingredients in PEG-3350, sodium chloride, sodium bicarbonate and potassium chloride for oral solution?

Active ingredients: polyethylene glycol 3350, sodium bicarbonate, sodium chloride, and potassium chloride.

Inactive ingredients: lemon-lime flavoring

Affordable Pharmaceuticals, LLC
Braintree, MA 02185, USA

This Medication Guide has been approved by the U.S. Food and Drug Administration.

Revised 5/2021

Principal Display Panel – Bottle Label

FILL TO THE TOP OF THE LINE ON BOTTLE

NDC 10572-302-01

TO PHARMACIST AND PATIENT: Mixing information is on base
label. Package insert may be
removed before dispensing.

Lemon-Lime Flavor
PEG-3350, Sodium Chloride,
Sodium Bicarbonate
and Potassium Chloride
for Oral Solution

When reconstituted with water to a volume of 4 liters, this solution contains PEG-3350 31.3 mmol/L, sodium 65 mmol/L, chloride 53 mmol/L, bicarbonate 17 mmol/L and potassium 5 mmol/L

Each disposable jug contains, in powdered form: polyethylene glycol 3350 420 g, sodium bicarbonate 5.72 g, sodium chloride 11.2 g, potassium chloride 1.48 g, flavor ingredients 2.0 g.

RX ONLY

Affordable
Pharmaceuticals LLC

Braintree, MA 02185 Rev 09/13